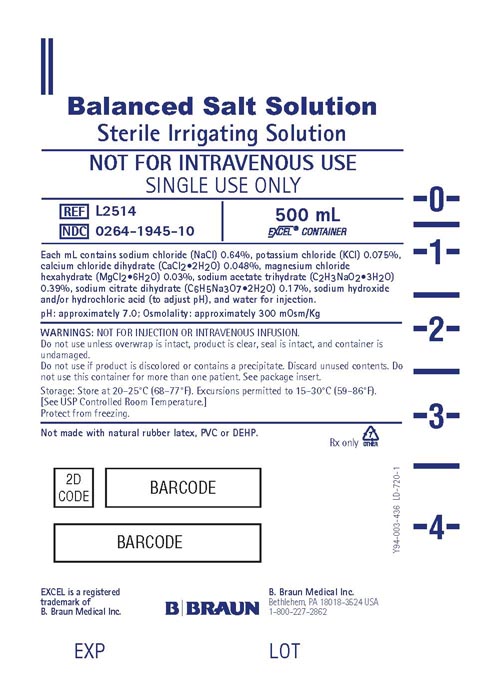 DRUG LABEL: Balanced Salt
NDC: 0264-1945 | Form: SOLUTION
Manufacturer: B. Braun Medical Inc.
Category: prescription | Type: HUMAN PRESCRIPTION DRUG LABEL
Date: 20240313

ACTIVE INGREDIENTS: SODIUM CHLORIDE 6.4 mg/1 mL; POTASSIUM CHLORIDE 0.75 mg/1 mL; CALCIUM CHLORIDE 0.48 mg/1 mL; MAGNESIUM CHLORIDE 0.3 mg/1 mL; SODIUM ACETATE 3.9 mg/1 mL; SODIUM CITRATE 1.7 mg/1 mL
INACTIVE INGREDIENTS: SODIUM HYDROXIDE; HYDROCHLORIC ACID; WATER

Balanced Salt Solution
Sterile Irrigating Solution

Y36-003-042 LD-721-1

Package Insert

EXCEL® CONTAINER

Rx only

DESCRIPTION

Balanced Salt Solution Sterile Irrigating Solution is a sterile balanced salt solution in 500 mL single-dose EXCEL® flexible containers. Each mL contains sodium chloride (NaCl) 0.64%, potassium chloride (KCl) 0.075%, calcium chloride dihydrate (CaCl2·2H2O) 0.048%, magnesium chloride hexahydrate (MgCl2·6H2O) 0.03%, sodium acetate trihydrate (C2H3NaO2·3H2O) 0.39%, sodium citrate dihydrate (C6H5Na3O7·2H2O) 0.17%, sodium hydroxide and/or hydrochloric acid (to adjust pH), and water for injection.

The pH is approximately 7.0.

The osmolality is approximately 300 mOsm/Kg.

The EXCEL® plastic container is made from a multilayered film. The solution contact layer is a rubberized copolymer of ethylene and propylene. The container is nontoxic and biologically inert. The container-solution unit is a closed system and is not dependent upon entry of external air during administration. The container is overwrapped to provide protection from the physical environment and to provide an additional moisture barrier when necessary.

Addition of medication should be accomplished using complete aseptic technique.

The closure system has two ports; the one for the administration set has a tamper evident plastic protector and the other is a medication addition site. Refer to the Directions for Use of the container.

CLINICAL PHARMACOLOGY

Balanced Salt Solution Sterile Irrigating Solution is an isotonic solution for use in irrigating tissues of the eyes.

INDICATIONS AND USAGE

For use as an extraocular and intraocular irrigating solution during ocular surgical procedure involving perfusion of the eye with an expected maximum duration of less than 60 minutes.

WARNINGS

- NOT FOR INJECTION OR INTRAVENOUS INFUSION.
- Do not use unless overwrap is intact, product is clear, seal is intact, and container is undamaged.
- Do not use if product is discolored or contains a precipitate.
- SINGLE patient use only. The contents of this container should not be used in more than one patient.
- This solution contains no preservative, unused contents should be discarded.

PRECAUTIONS

Open under aseptic conditions only.

Studies suggest that intraocular irrigating solutions which are iso-osmotic with normal aqueous fluids should be used with caution in diabetic patients undergoing vitrectomy since intraoperative lens changes have been observed.

There have been reports of corneal clouding or edema following ocular surgery in which Balanced Salt Solution Sterile Irrigating Solution was used as an irrigating solution.

ADVERSE REACTIONS

Irrigation or any other trauma to the corneal endothelium may result in corneal swelling or bullous keratopathy.

Post-operative inflammatory reactions as well as incidents of corneal edema and corneal decompensation have been reported.

DOSAGE AND ADMINISTRATION

The irrigating solution should be used according to standard format for each surgical procedure. Follow directions of the particular administration set to be used. Allow the fluid to flow and remove air from the tubing before irrigation begins.

HOW SUPPLIED

Balanced Salt Solution Sterile Irrigating Solution is supplied in sterile and nonpyrogenic 500 mL single-dose EXCEL® flexible containers with clear overwrap, 24 per case.

Not made with natural rubber latex, PVC or DEHP.

NDC | REF | Size
Balanced Salt Solution Sterile Irrigating Solution
0264-1945-10 | L2514 | 500 mL

STORAGE

Store at 20–25°C (68–77°F). Excursions permitted to 15–30°C (59–86°F). [See USP Controlled Room Temperature.] Protect from freezing.

Revised: August 2021

EXCEL® is a registered trademark of B. Braun Medical Inc.

Directions for Use of EXCEL® Container

Caution: Do not use plastic containers in series connection.

To Open

Tear overwrap down at notch and remove solution container. Check for minute leaks by squeezing solution container firmly. If leaks are found, discard solution as sterility may be impaired.

NOTE: Before use, perform the following checks:

Inspect each container. Read the label. Ensure solution is the one ordered and is within the expiration date. Invert container and carefully inspect the solution in good light for cloudiness, haze, or particulate matter. Any container which is suspect should not be used.

Use only if solution is clear and container and seals are intact.

Preparation for Administration

1. Remove plastic protector from sterile set port at bottom of container.
2. Attach administration set. Refer to complete directions accompanying set.

To Add Medication

Warning: Some additives may be incompatible.

To Add Medication Before Solution Administration

1. Prepare medication site.
2. Using syringe with 18–22 gauge needle, puncture medication port and inner diaphragm and inject.
3. Squeeze and tap ports while ports are upright and mix solution and medication thoroughly.

To Add Medication During Solution Administration

1. Close clamp on the set.
2. Prepare medication site.
3. Using syringe with 18–22 gauge needle of appropriate length (at least 5/8 inch), puncture resealable medication port and inner diaphragm and inject.
4. Remove container from IV pole and/or turn to an upright position.
5. Evacuate both ports by tapping and squeezing them while container is in the upright position.
6. Mix solution and medication thoroughly.
7. Return container to in use position and continue administration.

B. Braun Medical Inc.

Bethlehem, PA 18018-3524 USA
1-800-227-2862

PRINCIPAL DISPLAY PANEL - 500 mL Label

Balanced Salt Solution
Sterile Irrigating Solution

NOT FOR INTRAVENOUS USE
SINGLE USE ONLY

REF L2514

NDC 0264-1945-10

500 mL
EXCEL® CONTAINER

Each mL contains sodium chloride (NaCl) 0.64%, potassium chloride (KCl) 0.075%,
calcium chloride dihydrate (CaCl2·2H2O) 0.048%, magnesium chloride
hexahydrate (MgCl2·6H2O) 0.03%, sodium acetate trihydrate (C2H3NaO2·3H2O)
0.39%, sodium citrate dihydrate (C6H5Na3O7·2H2O) 0.17%, sodium hydroxide
and/or hydrochloric acid (to adjust pH), and water for injection.

pH: approximately 7.0; Osmolality: approximately 300 mOsm/Kg

WARNINGS: NOT FOR INJECTION OR INTRAVENOUS INFUSION.
Do not use unless overwrap is intact, product is clear, seal is intact, and container is undamaged.
Do not use if product is discolored or contains a precipitate. Discard unused contents. Do not use
this container for more than one patient. See package insert.

Storage: Store at 20-25°C (68-77°F). Excursions permitted to 15-30°C (59-86°F).
[See USP Controlled Room Temperature.]
Protect from freezing.

Not made with natural rubber latex, PVC or DEHP.

Rx only

Y94-003-436 LD-720-1

EXCEL is a registered trademark of B. Braun Medical Inc.

B. Braun Medical Inc.
Bethlehem, PA 18018-3524 USA
1-800-227-2862

Y94-003-436